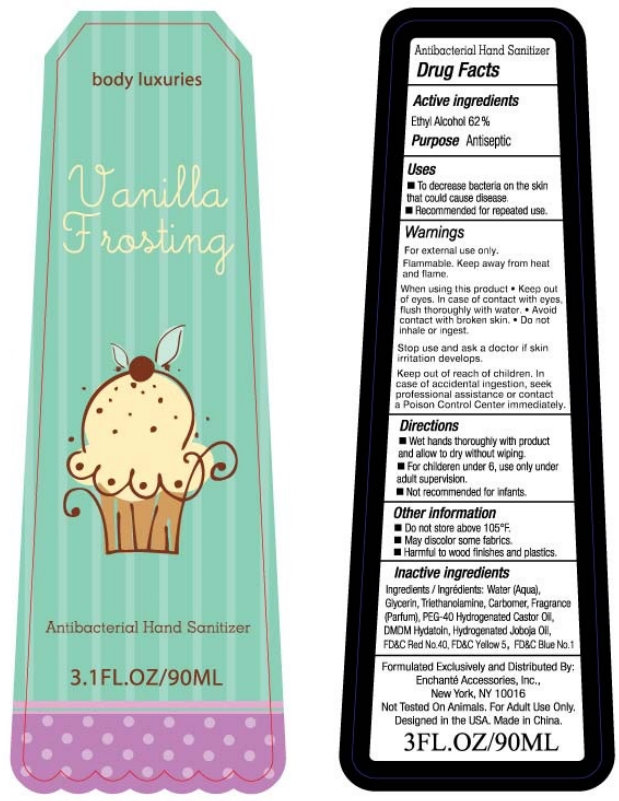 DRUG LABEL: body luxuries Vanilla Frosting Antibacterial Hand Sanitizer
NDC: 50563-500 | Form: LIQUID
Manufacturer: Enchante Accessories, Inc.
Category: otc | Type: HUMAN OTC DRUG LABEL
Date: 20110120

ACTIVE INGREDIENTS: ALCOHOL  62 mL/100 mL
INACTIVE INGREDIENTS: WATER; GLYCERIN; TROLAMINE; POLYOXYL 40 HYDROGENATED CASTOR OIL; DMDM HYDANTOIN; JOJOBA OIL; FD&C RED NO. 40; FD&C YELLOW NO. 5; FD&C BLUE NO. 1

body luxuries Vanilla Frosting Antibacterial Hand Sanitizer

Antibacterial Hand Sanitizer

Drug Facts

Active Ingredients

Ethyl Alcohol 62%

Purpose

Antiseptic

Uses

- To decrease bacteria on the skin that could cause disease.
- Recommended for repeated use.

Warnings

For external use only.

Flammable. Keep away from heat and flame.

When using this product

- Keep out of eyes. In case of contact with eyes, flush thoroughly with water.
- Avoid contact with broken skin.
- Do not inhale or ingest.

Stop use and ask a doctor if skin irritation develops.

KEEP OUT OF REACH OF CHILDREN

Keep out reach of children. In case of accidental ingestion, seek professional assistance or contact a Poison Control Center immediately.

Directions

- Wet hands thoroughly with product and allow to dry without wiping.
- For children under 6, use only under adult supervision.
- Not recommended for infants.

Other Information

- Do not store above 105 degrees F
- May discolor some fabrics.
- Harmful to wood finishes and plastics.

Inactive ingredients

Water (Aqua), Glycerin, Triethanolamine, Carbomer, Fragrance (Parfum), PEG-40 Hydrogenated Castor Oil, DMDM Hydantoin, Hydrogenated Jojoba Oil, FD and C Red No.40, FD and C Yellow 5, FD and C Blue No.1

Formulated Exclusively and Distributed By:

Enchante Accessories, Inc.,

New York, NYm 10016

Not Tested On Animals, For Adult Use Only.

Designed in the USA. Made in China

3 FL. OZ / 90ML

PACKAGE LABEL

body luxuries

Vanilla Frosting

Antibacterial Hand Sanitizer

3.1 FL. OZ / 90ML